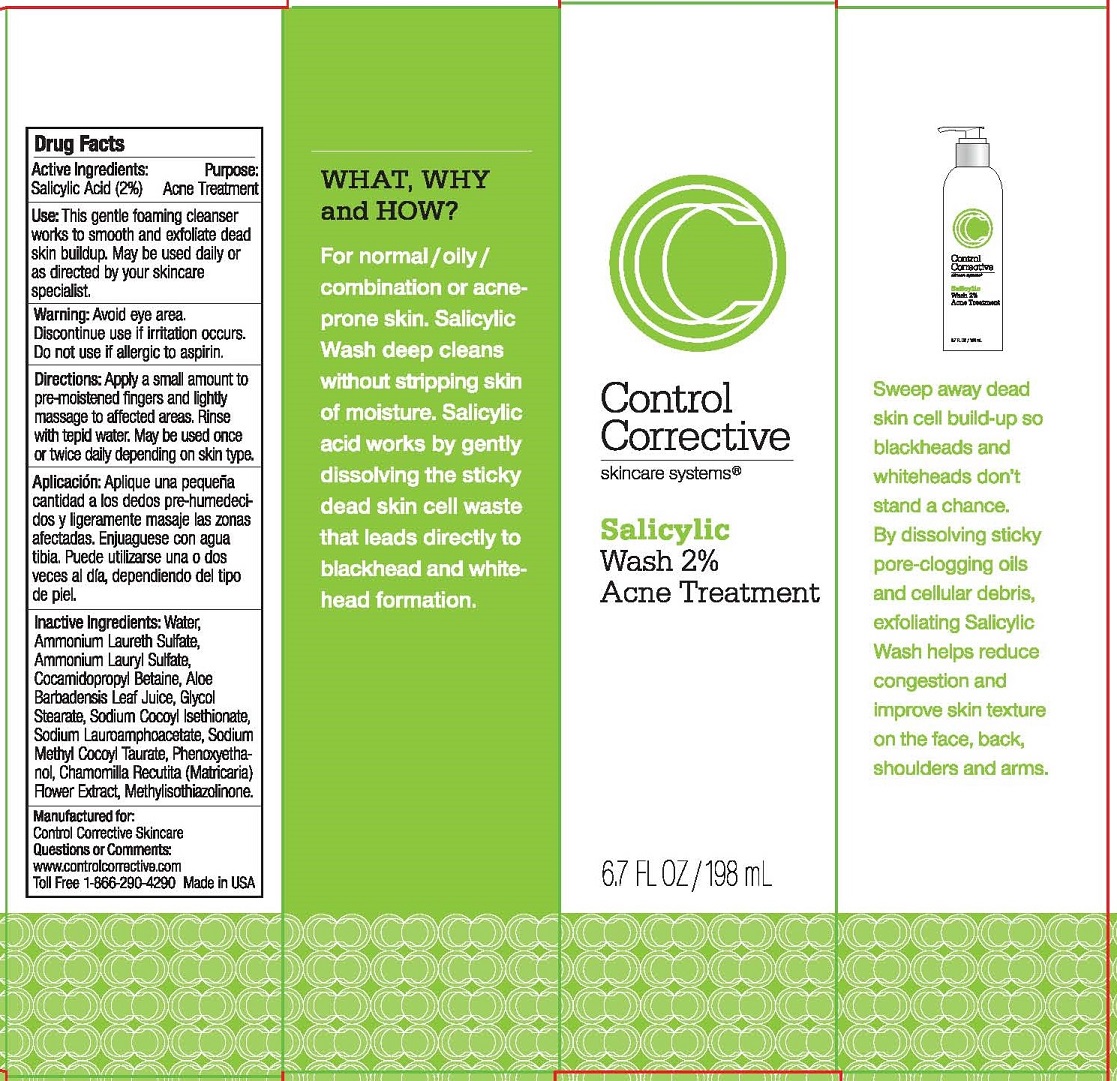 DRUG LABEL: SALICYLIC WASH
NDC: 70764-102 | Form: LOTION
Manufacturer: CONTROL CORRECTIVE SKINCARE INC
Category: otc | Type: HUMAN OTC DRUG LABEL
Date: 20251231

ACTIVE INGREDIENTS: SALICYLIC ACID 2 g/100 mL
INACTIVE INGREDIENTS: WATER; AMMONIUM LAURETH-2 SULFATE; AMMONIUM LAURYL SULFATE; COCAMIDOPROPYL BETAINE; ALOE VERA LEAF; GLYCOL STEARATE; SODIUM COCOYL ISETHIONATE; SODIUM LAUROAMPHOACETATE; SODIUM METHYL COCOYL TAURATE; PHENOXYETHANOL; CHAMOMILE; METHYLISOTHIAZOLINONE

CONTROL CORRECTIVE - SALICYLIC WASH 2% ACNE TREATMENT (70764-102)

ACTIVE INGREDIENTS

SALICYLIC ACID (2.0%)

PURPOSE

ACNE TREATMENT

USE

THIS GENTLE FOAMING CLEANSER WORKS TO SMOOTH AND EXFOLIATE DEAD SKIN BUILDUP. MAY BE USED DAILY OR AS DIRECTED BY YOUR SKINCARE SPECIALIST.

WARNINGS

AVOID EYE AREA. DISCONTINUE USE IF IRRITATION OCCURS. DO NOT USE IF ALLERGIC TO ASPERIN.

DIRECTIONS

APPLY A SMALL AMOUNT TO PRE-MOISTENED FINGERS AND LIGHTLY MASSAGE TO AFFECTED AREAS. RINSE WITH TEPID WATER. MAY BE USED ONCE OR TWICE DAILY DEPENDING ON SKIN TYPE.

INACTIVE INGREDIENTS

WATER, AMMONIUM LAURETH SULFATE, AMMONIUM LAURYL SULFATE, COCAMIDOPROPYL BETAINE, ALOE BARBADENSIS LEAF JUICE, GLYCOL STEARATE, SODIUM COCOYL ISETHIONATE, SODIUM LAUROAMPHOACETATE, PHENOXYETHANOL, CHAMOMILE RECUTITA (MATRICARIA) FLOWER EXTRACT, METHYLISOTHIAZOLINONE.

KEEP OUT OF REACH OF CHILDREN.

QUESTIONS OR COMMENTS

WWW.CONTROLCORRECTIVE.COM

TOLL FREE 1-866-290-4290 MADE IN USA